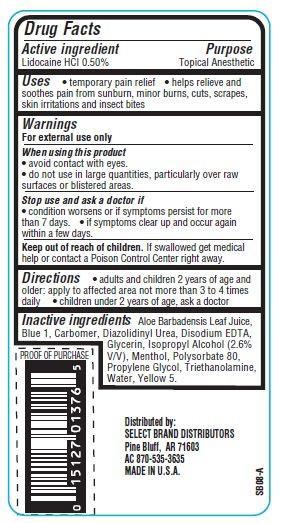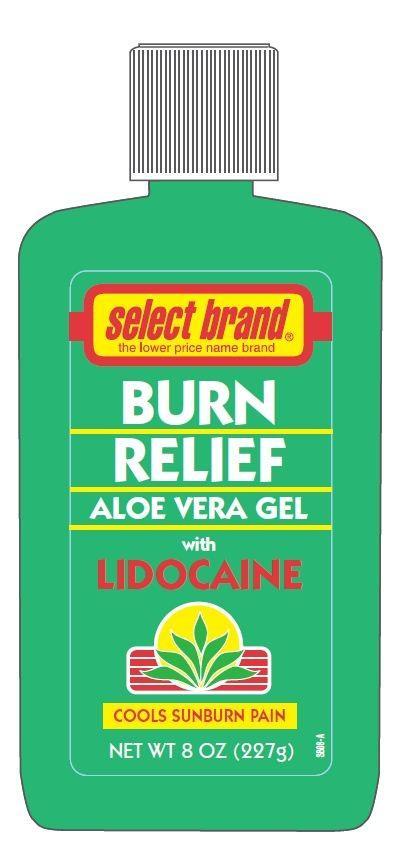 DRUG LABEL: Select Brand Burn Relief
NDC: 15127-002 | Form: GEL
Manufacturer: Select Brand Distributors
Category: otc | Type: HUMAN OTC DRUG LABEL
Date: 20121119

ACTIVE INGREDIENTS: LIDOCAINE HYDROCHLORIDE 0.5 g/100 g
INACTIVE INGREDIENTS: ALOE VERA LEAF; FD&C BLUE NO. 1; DIAZOLIDINYL UREA; EDETATE DISODIUM; GLYCERIN; MENTHOL; POLYSORBATE 80; PROPYLENE GLYCOL; TROLAMINE; WATER; FD&C YELLOW NO. 5

Drug Facts

Active ingredient

Lidocaine HCL 0.50%

Purpose

Topical Anesthetic

Uses

- temporary relief of pain and itching
- helps relieve and soothes pain from sunburn, minor burns,cuts,scrapes, skin irritations and insect bites

Warnings

For external use only

When using this product

- avoid contact with eyes.
- do not use in large quantities, particularly over raw surfaces or blistered areas

Stop use and ask a doctor if

- condition worsens or if symptoms persist for more than 7 days.
- if symptoms clear up and occur again within a few days.

Keep out of reach of children.
If swallowed get medical help or contact Poison Control Center immediately.

Directions

- adults and children 2 years of age and older: apply to affected area not more than 3 to 4 times daily
- children under 2 years of age: ask a doctor

Inactive ingredients

Water, Propylene Glycol, Glycerin, Isopropyl Alcohol, Triethanolamine, Polysorbate 80, Carbomer, Aloe Barbadensis Leaf Juice, Menthol, Disodium EDTA, Diazolidinyl Urea, Yellow 5, Blue 1.

Principal Display Panel

select brand
the lower price name brand
BURN RELIEF
ALOE VERA GEL
with
LIDOCAINE
COOLS SUNBURN PAIN
NET WT 8 OZ(227g)